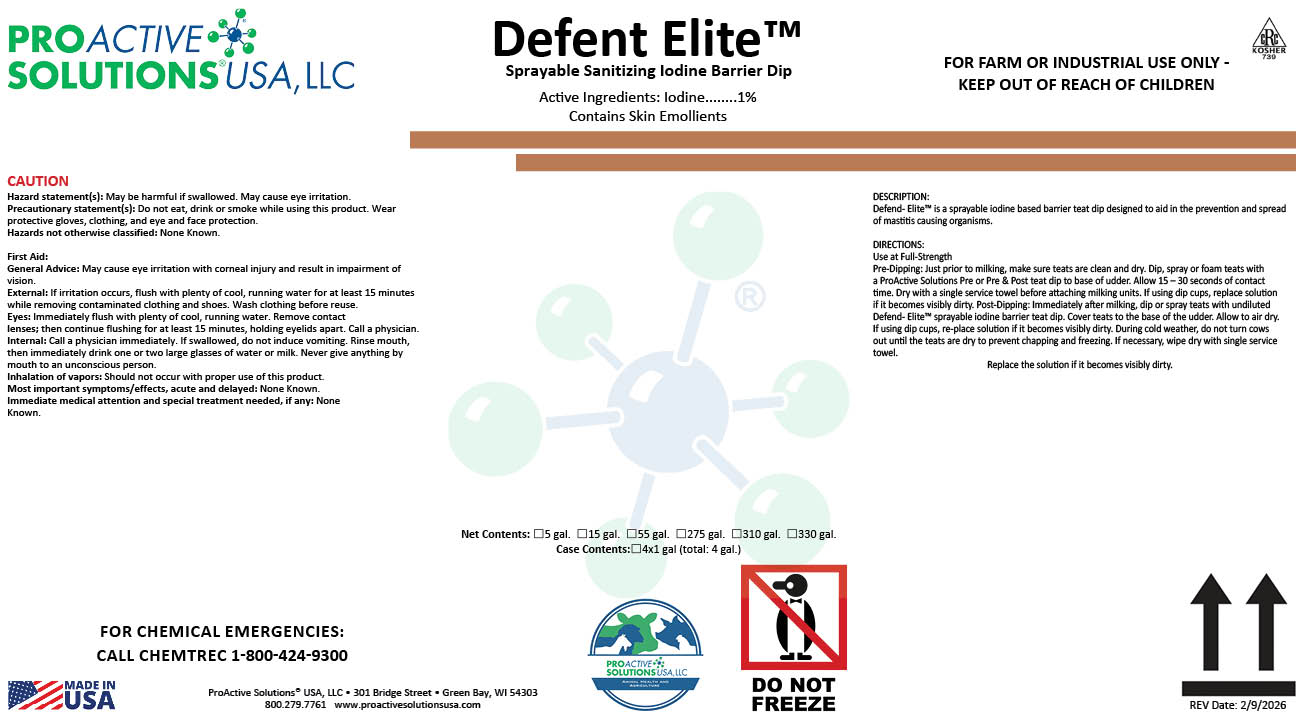 DRUG LABEL: Defend Elite
NDC: 63927-4125 | Form: LIQUID
Manufacturer: ProActive Solutions USA, LLC
Category: animal | Type: OTC ANIMAL DRUG LABEL
Date: 20260210

ACTIVE INGREDIENTS: IODINE 1 kg/100 kg

Defend Elite

Defend Elite

DESCRIPTION:
Defend- Elite™ is a sprayable iodine based barrier teat dip designed to aid in the prevention and spread
of mastitis causing organisms.
DIRECTIONS:
Use at Full-Strength
Pre-Dipping: Just prior to milking, make sure teats are clean and dry. Dip, spray or foam teats with
a ProActive Solutions Pre or Pre & Post teat dip to base of udder. Allow 15 – 30 seconds of contact
time. Dry with a single service towel before attaching milking units. If using dip cups, replace solution
if it becomes visibly dirty. Post-Dipping: Immediately after milking, dip or spray teats with undiluted
Defend- Elite™ sprayable iodine barrier teat dip. Cover teats to the base of the udder. Allow to air dry.
If using dip cups, re-place solution if it becomes visibly dirty. During cold weather, do not turn cows
out until the teats are dry to prevent chapping and freezing. If necessary, wipe dry with single service
towel.
Replace the solution if it becomes visibly dirty.

Hazard statement(s): May be harmful if swallowed. May cause eye irritation.
Precautionary statement(s): Do not eat, drink or smoke while using this product. Wear
protective gloves, clothing, and eye and face protection.
Hazards not otherwise classified: None Known.
First Aid:
General Advice: May cause eye irritation with corneal injury and result in impairment of
vision.
External: If irritation occurs, flush with plenty of cool, running water for at least 15 minutes
while removing contaminated clothing and shoes. Wash clothing before reuse.
Eyes: Immediately flush with plenty of cool, running water. Remove contact
lenses; then continue flushing for at least 15 minutes, holding eyelids apart. Call a physician.
Internal: Call a physician immediately. If swallowed, do not induce vomiting. Rinse mouth,
then immediately drink one or two large glasses of water or milk. Never give anything by
mouth to an unconscious person.
Inhalation of vapors: Should not occur with proper use of this product.
Most important symptoms/effects, acute and delayed: None Known.
Immediate medical attention and special treatment needed, if any: None
Known.